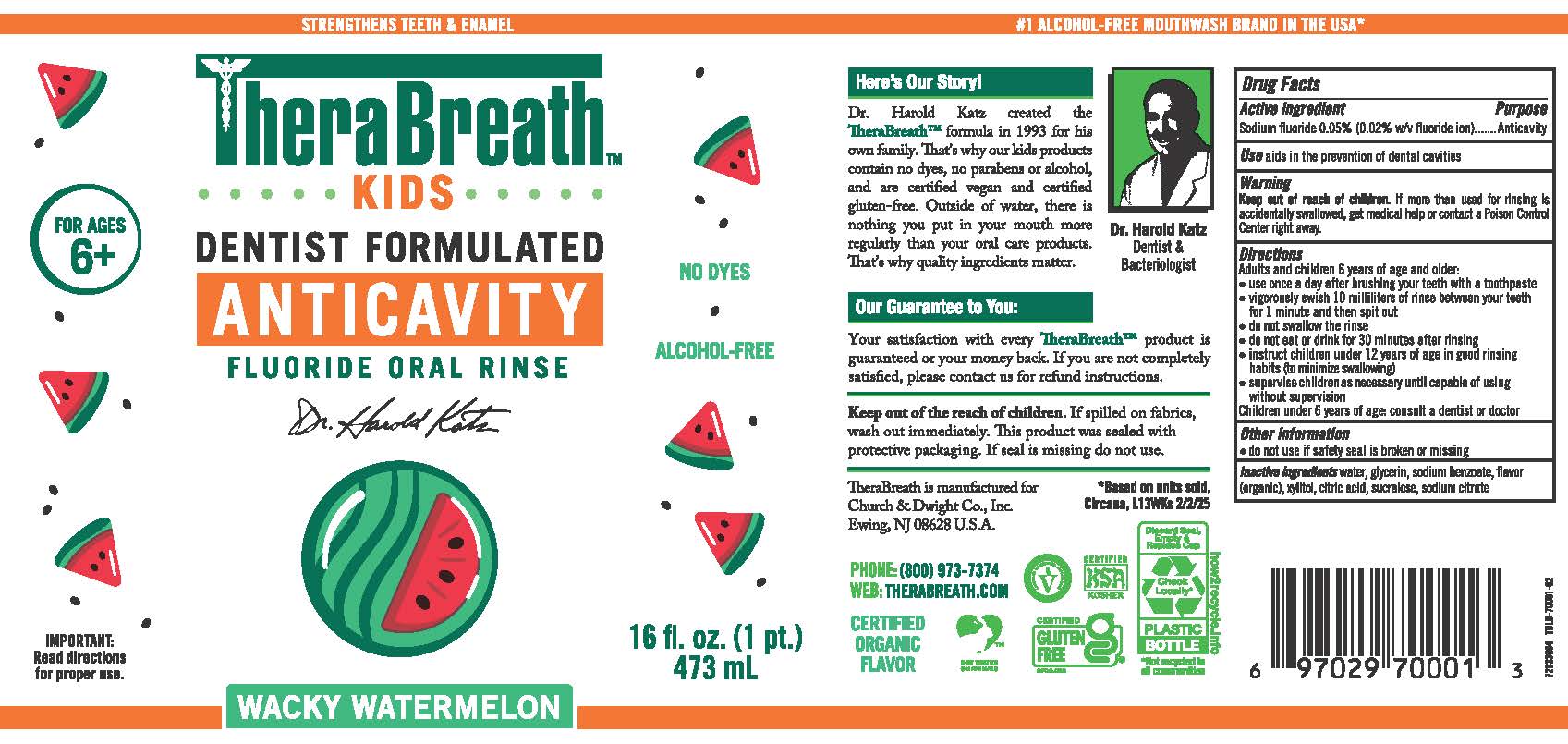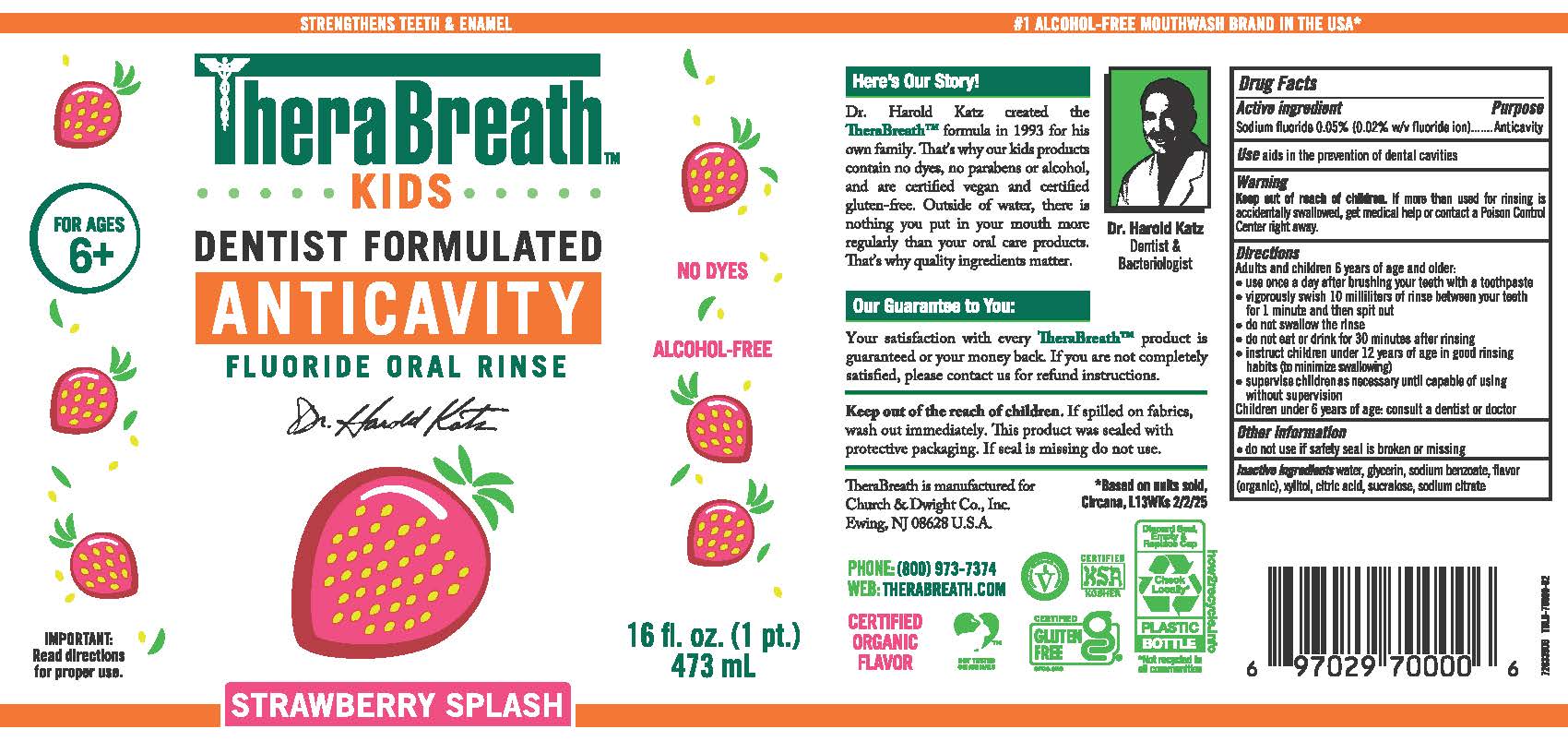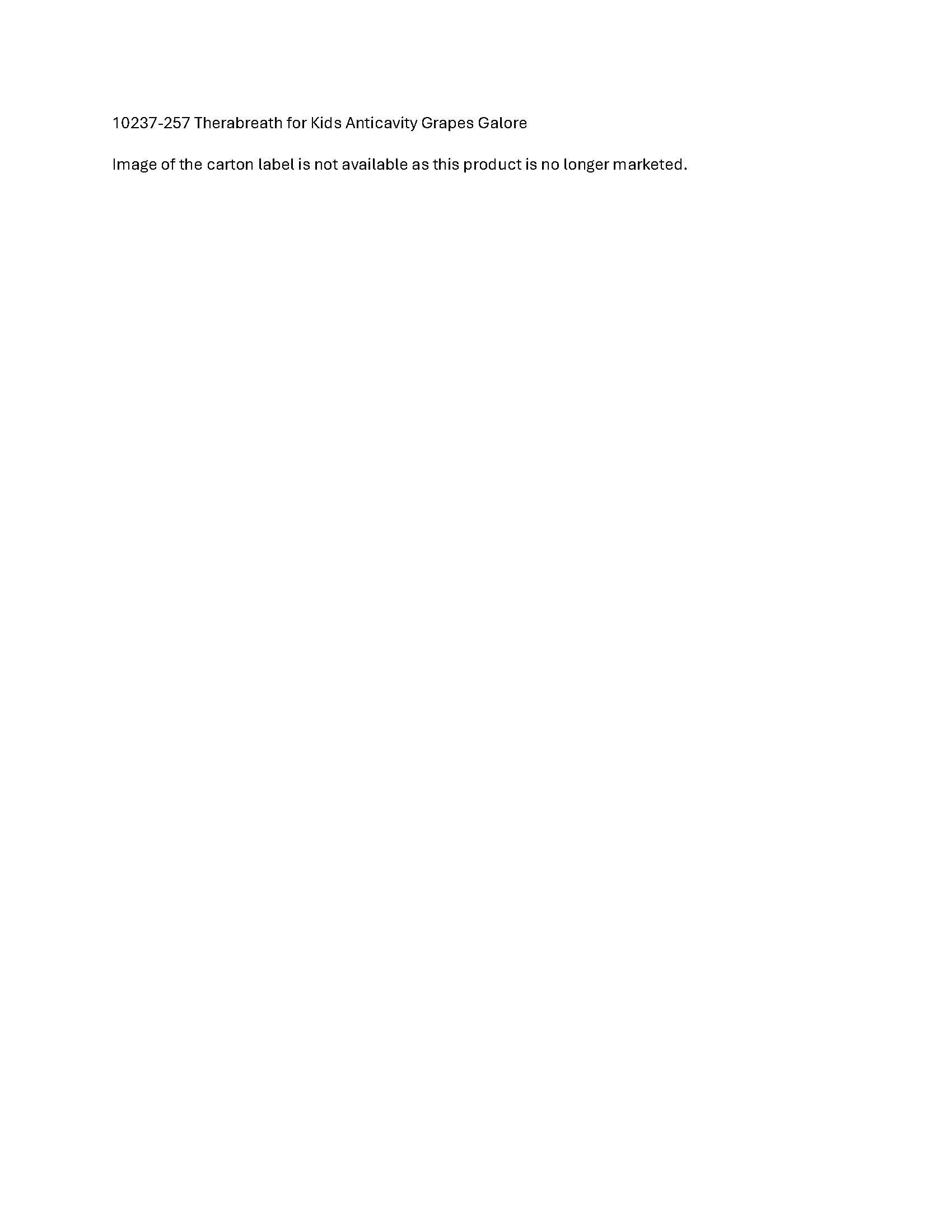 DRUG LABEL: TheraBreath for Kids Anticavity Wacky Watermelon
NDC: 10237-255 | Form: RINSE
Manufacturer: Church & Dwight Co., Inc.
Category: otc | Type: HUMAN OTC DRUG LABEL
Date: 20251125

ACTIVE INGREDIENTS: SODIUM FLUORIDE 0.5 mg/1 mL
INACTIVE INGREDIENTS: WATER; GLYCERIN; SODIUM BENZOATE; CITRIC ACID MONOHYDRATE; SUCRALOSE; SODIUM CITRATE, UNSPECIFIED FORM

TheraBreath™for Kids Anticavity Oral Rinse

Drug Facts

Active Ingredients

Sodium Fluoride 0.05% (0.02% w/v fluoride ion)

Purpose

Anticavity

Use

Aids in the prevention of dental cavities

Warnings

Keep out of reach of children. If more than used for rinsing is accidentally swallowed, get medical help or contact a Poison Control Center right away.

Directions

Adults and children 6 years of age and older:

- use once a day after brushing your teeth with a toothpaste
- vigorously swish 10 milliliters of rinse between your teeth for 1 minute and then spit out
- do not swallow the rinse
- do not eat or drink for 30 minutes after rinsing.
- instruct children under 12 years of age in good rinsing habits (to minimize swallowing)
- supervise children as necessary until capable of using without supervision.

Children under 6 years of age: Consult a dentist or doctor.

Other information

- Do not use if safety seal is broken or missing

Inactive Ingredients

water, glycerin, sodium benzoate, flavor (organic), xylitol, citric acid, sucralose, sodium citrate

PRINCIPAL DISPLAY PANEL - 473 mL Bottle Label - WACKY WATERMELON

STRENGTHENS TEETH & ENAMEL

THERABREATH

KIDS

FOR AGES 6+

DENTIST FORMULATED

ANTICAVITY

FLUORIDE ORAL RINSE

Dr. Harold Katz

WACKY WATERMELON

16 fl. oz. (1 pt.) 473 mL

PRINCIPAL DISPLAY PANEL - 473 mL Bottle Label - STRAWBERRY SPLASH

STRENGTHENS TEETH & ENAMEL

THERABREATH

KIDS

FOR AGES 6+

DENTIST FORMULATED

ANTICAVITY

FLUORIDE ORAL RINSE

Dr. Harold Katz

16 fl. oz. (1 pt.) 473 mL

STRAWBERRY SPLASH

PACKAGE LABEL

10237-257 Therabreath for Kids Anticavity Grapes Galore

Image of the carton label is not available as this product is no longer marketed.